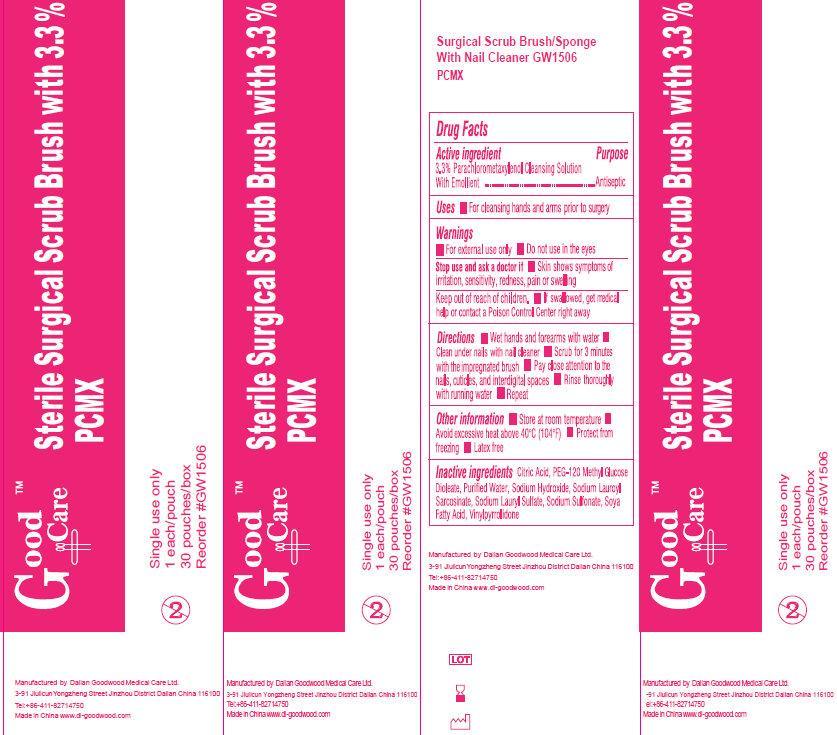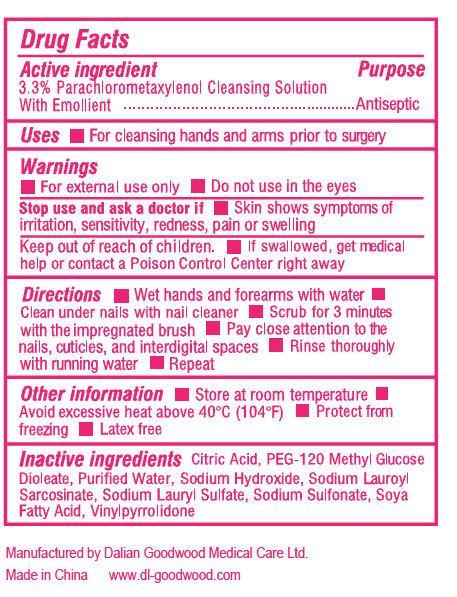 DRUG LABEL: Good Care Sterile Scrub Brush with PCMX
NDC: 50685-008 | Form: SOLUTION
Manufacturer: Dalian Goodwood Medical Care Ltd.
Category: otc | Type: HUMAN OTC DRUG LABEL
Date: 20230525

ACTIVE INGREDIENTS: CHLOROXYLENOL 33 mg/1 mL
INACTIVE INGREDIENTS: CITRIC ACID MONOHYDRATE; PEG-120 METHYL GLUCOSE DIOLEATE; WATER; SODIUM HYDROXIDE; SODIUM LAUROYL SARCOSINATE; SODIUM LAURYL SULFATE; SOYBEAN; POLYQUATERNIUM-16 (N-VINYLPYRROLIDINONE:3-METHYL-1-VINYLIMIDAZOLIUM CHLORIDE (5:5))

Good Care Sterile Scrub Brush with 3.3% PCMX

Active Ingredient

3.3% Parachlorometaxylenol Cleansing Solution With Emollient

Purpose

Antiseptic

Uses

- For cleansing hands and arms prior to surgery

Warnings

- For external use only
- Do not use in eyes

Stop use and ask a doctor if

- skin shows symptoms of irritation, sensitivity, redness, pain or swelling

Keep out of reach of children.

- If swallowed, get medical help or contact a Poison Control right away

Directions

- Wet hands and forearms with water
- Clean under nails with nail cleaner
- Scrub for 3 minutes with the impregnated brush
- Pay close attention to the nails, cuticles, and interdigital spaces
- Rinse thoroughly with running water
- Repeat

Other Information

- Store at room temperature
- Avoid excessive heat above 40 degrees C (104 degrees F)
- Protect from freezing
- Latex free

Inactive Ingredients

Citric Acid, PEG -120 Methyl Glucose Dioleate, Purified Water, Sodium Hydroxide, Sodium Lauroyl Sarcosinate, Sodium Lauryl Sulfate, Sodium Sulfonate, Soya Fatty Acid, Vinylpyrrolidone

Manufactured by Dalian Goodwood Medical Care Ltd.

Made in China